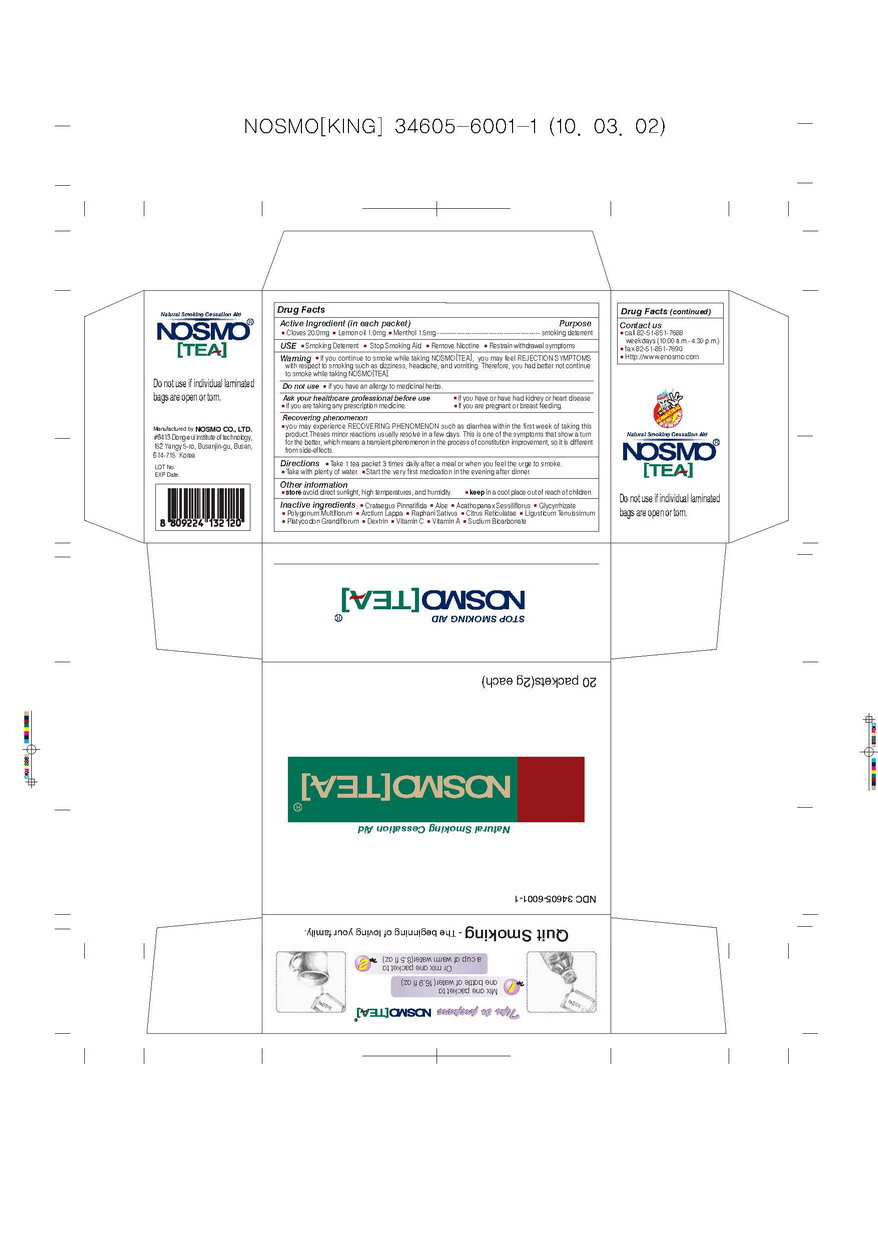 DRUG LABEL: Nosmotea
NDC: 34605-6001 | Form: POWDER
Manufacturer: Nosmo Co., Ltd
Category: otc | Type: HUMAN OTC DRUG LABEL
Date: 20100306

ACTIVE INGREDIENTS: clove 20 mg/1 g; lemon 1 mg/1 g; menthol 1.5 mg/1 g

Drug Facts

Active Ingredients: Cloves, Lemon oil, Menthol

DESCRIPTION

USE ■ Smoking Deterrent ■ Stop Smoking Aid ■ Remove Nicotine ■ Restrain withdrawal symptoms
If you continue to smoke while taking Nosmotea, you may feel REJECTION SYMPTOMS
with respect to smoking such as dizziness, headache, and vomiting. Therefore, you had better not continue
to smoke while taking Nosmotea
Do not use if you have an allergy to medicinal herbs.
■ if you are taking any prescription medicine. ■ if you are pregnant or breast feeding.
Recovering phenomenon
■ you may experience RECOVERING PHENOMENON such as diarrhea within the first week of taking this product.
Theses minor reactions usually resolve in a few days. This is one of the symptoms that show a turn for the better,
which means a transient phenomenon in the process of constitution improvement, so it is different from side-effects.
Directions
■ You can conveniently drink it after dissolving Nosmotea in a cup of warm water (200mL). Take a tea bag
three times a day after having a meal or on feeling like to smoke for 4-5 weeks. However, do not take more than
4 tea bag a day. Start the very first medication in the evening after dinner.
Other information
store avoid direct sunlight,
high temperatures, and humid ity.
keep in a cool place out of reach of children.